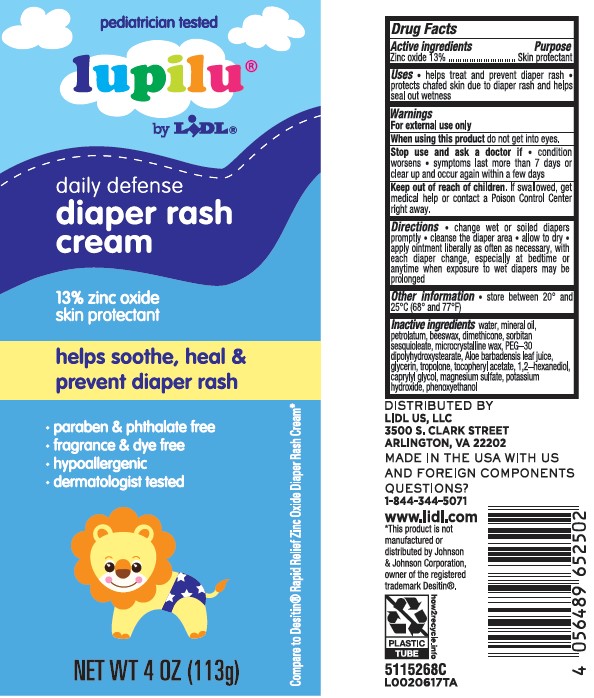 DRUG LABEL: Diaper Rash
NDC: 71141-622 | Form: CREAM
Manufacturer: Lidl US, LLC
Category: otc | Type: HUMAN OTC DRUG LABEL
Date: 20260204

ACTIVE INGREDIENTS: ZINC OXIDE 130 mg/1 g
INACTIVE INGREDIENTS: WATER; MINERAL OIL; PETROLATUM; YELLOW WAX; DIMETHICONE; SORBITAN SESQUIOLEATE; MICROCRYSTALLINE WAX; PEG-30 DIPOLYHYDROXYSTEARATE; ALOE VERA LEAF; GLYCERIN; TROPOLONE; .ALPHA.-TOCOPHEROL ACETATE; 1,2-HEXANEDIOL; CAPRYLYL GLYCOL; MAGNESIUM SULFATE MONOHYDRATE; POTASSIUM HYDROXIDE; PHENOXYETHANOL

Lupilu 226.002/226AD
Creamy Diaper Rash Ointment

Active Ingredient

Zinc oxide 13%

Purpose

Skin protectant

Uses

- helps treat and prevent diaper rash
- protects chafed skin due to diaper rash and helps seal out wetness

Warnings

For external use only

When using this product

- do not get into eyes

Stop use and ask a doctor if

- condition worsens
- symptoms last more than 7 days or clear up and occur again within a few days

Keep out of reach of children.

If swallowed, get medical help or contact a Poison Control Center right away.

Directions

- change wet and soiled diapers promptly
- cleanse the diaper area
- allow to dry
- apply ointment liberally as often as necessary, with each diaper change, especially at bedtime or anytime when exposure to wet diapers may be prolonged

Other Information

store between 20º and 25ºC (68º and 77º F)

Inactive ingredients

water, mineral oil, petrolatum, beeswax, dimethicone, sorbitan sesquioleate, microcrystalline wax, PEG-30 dipolyhydroxystearate, Aloe barbadensis leaf juice, glycerin, tropolone, tocopheryl acetate, 1,2-hexanediol, caprylyl glycol, magnesium sulfate, potassium hydroxide, phenoxyethanol

ADVERSE REACTION

DISTRIBUTED BY

LIDL US, LLC

3500 S. CLARK STREET

ARRLINGTON, VA 22202

MADE IN THE USA WITH US AND FOREIGN COMPONENTS

QUESTIONS?

1-844-344-5071

www.lidl.com

how2recycle.info

Plastice Tube

Disclaimer

*This product is not manufactured or distributed by Johnson & Johnson Corporation, owner of the registered trademark Desitin.

Principal Panel Display

pediatrician tested

lupilu®

by LIDL®

daily defense

diaper rash cream

13% zinc oxide

skin protectant

helps soothe, heal & prevent diaper rash

- paraben & phthalate free
- fragrance & dye free
- hypoallergenic
- dermatologist tested

NET WE 4 OZ (113 g)

Compare to Desitin®Rapid Relief Oxide Diaper Rash Cream*